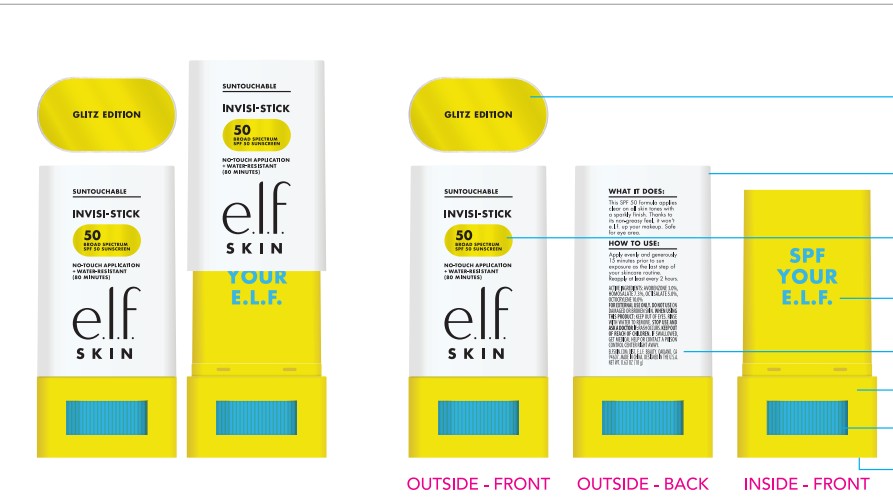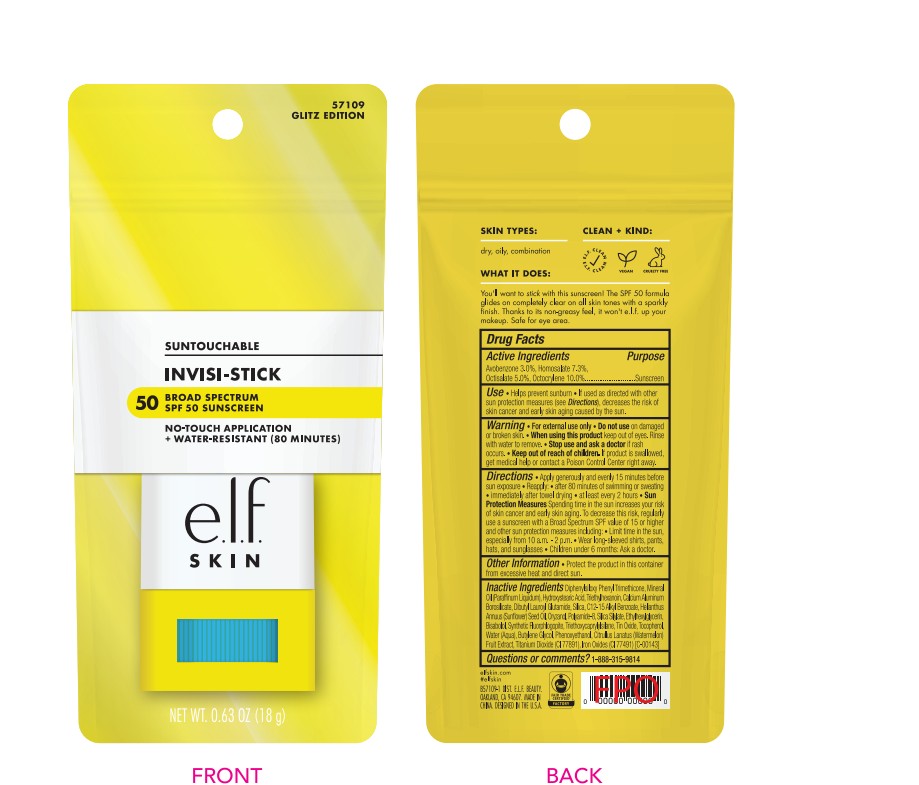 DRUG LABEL: e.l.f. Suntouchable Invisi-Stick Glitz SPF 50
NDC: 76354-457 | Form: STICK
Manufacturer: e.l.f cosmetics,Inc.
Category: otc | Type: HUMAN OTC DRUG LABEL
Date: 20260201

ACTIVE INGREDIENTS: OCTOCRYLENE 100 mg/1 g; HOMOSALATE 73 mg/1 g; OCTISALATE 50 mg/1 g; AVOBENZONE 30 mg/1 g
INACTIVE INGREDIENTS: FERRIC IRON OXIDE ADIPATE; DIPHENYLSILOXY PHENYL TRIMETHICONE; MINERAL OIL; 12-HYDROXYSTEARIC ACID; TRIETHYLHEXANOIN; DIBUTYL LAUROYL GLUTAMIDE; SILICON DIOXIDE; ALKYL (C12-15) BENZOATE; SUNFLOWER OIL; ORYZANOL; ETHYLHEXYLGLYCERIN; TRIETHOXYCAPRYLYLSILANE; TOCOPHEROL; WATER; BUTYLENE GLYCOL; PHENOXYETHANOL; WATERMELON; SILICA DIMETHYL SILYLATE; TITANIUM DIOXIDE; POLYAMIDE-8 (4500 MW); BISABOLOL; TIN OXIDE; FLUOROURACIL; CALCIUM ALUMINUM BOROSILICATE

e.l.f. Suntouchable Invisi-Stick Glitz SPF 50

Active Ingredients

Avobenzone 3.0%

Homosalate 7.3%

Octisalate 5.0%

Octocrylene 10.0%

Purpose

Sunscreen

Use

- Helps prevent sunburn
- If used as directed with other sun protection measures (see Directions), decreases the risk of skin cancer and early skin aging caused by the sun.

Warning

- For external use only.

• Do not use

on damaged or broken skin.

• When using this product

keep out of eyes. Rinse with water to remove.

• Stop use and ask a doctor

if rash occurs.

• Keep out of reach of children.

If product is swallowed, get medical help or contact a Poison Control Center right away.

Directions

- Apply generosuly and evenly 15 minutes before sun exposure
- Reapply:
- after 80 minutes of swimming or sweating
- immediately after towel drying
- at least every 2 hours
- Sun Protection MeasuresSpending time in the sun increases your risk of skin cancer and early skin aging. To decrease this risk, regularly use a sunscreen with a Broad Spectrum SPF value of 15 or higher and other sun protection measures including:
- Limit time in the sun, especially from 10 a.m. - 2 p.m.
- Wear long-sleeved shirts, pants, hats, and sunglasses
- Children under 6 months: Ask a doctor.

Other Information

- Protect the product in this container from excessive heat and direct sun.

Inactive Ingredients

Diphenylsiloxy Phenyl Trimethicone, Mineral Oil (Paraffinum Liquidum), Hydroxystearic Acid, Triethylhexanoin, Calcium Aluminum Borosilicate, Dibutyl Lauroyl Glutamide, Silica, C12-15 Alkyl Benzoate, Helianthus Annuus (Sunflower) Seed Oil, Oryzanol, Polyamide-8, Silica Silylate, Ethylhexylglycerin, Bisabolol, Synthetic Fluorphlogopite, Triethoxycaprylylsilane, Tin Oxide, Tocopherol, Water (Aqua), Butylene Glycol, Phenoxyethanol, Citrullus Lanatus (Watermelon) Fruit Extract, Titanium Dioxide (CI 77891), Iron Oxides (CI 77491) [C-00143]

Questions or comments?

1-888-315-9814